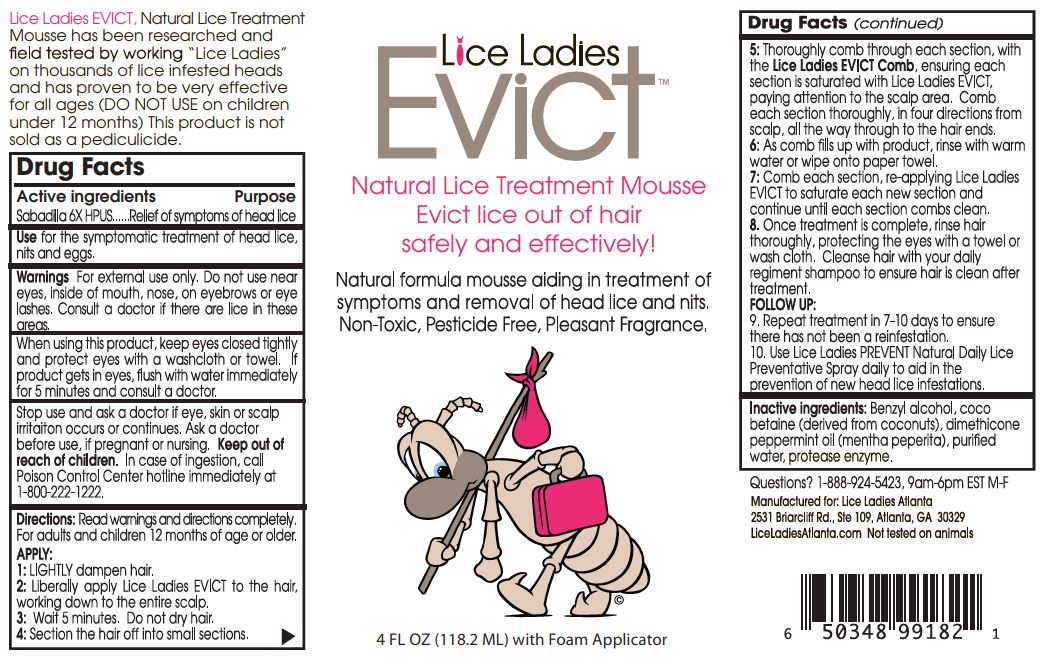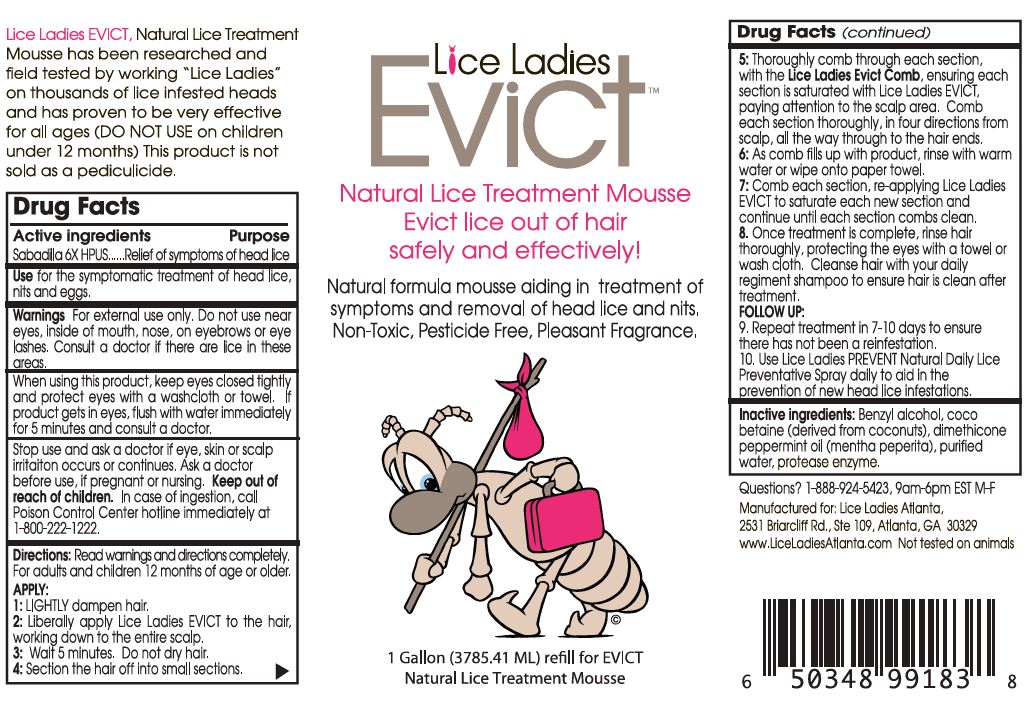 DRUG LABEL: EVICT
NDC: 70413-920 | Form: SOLUTION
Manufacturer: Lice Ladies Atlanta, LLC
Category: homeopathic | Type: HUMAN OTC DRUG LABEL
Date: 20251110

ACTIVE INGREDIENTS: SCHOENOCAULON OFFICINALE SEED 6 [hp_X]/1 mL
INACTIVE INGREDIENTS: BENZYL ALCOHOL; COCO-BETAINE; MENTHA X PIPERITA WHOLE; WATER; LIPROTAMASE PROTEASE

Lice Ladies EVICT

Active Ingredients Sabadilla 6X HPUS

Purpose Relief of symptoms of head lice

INDICATIONS AND USAGE

Use for the symptomatic treatment of head lice, nits and eggs.

WARNINGS

Warnings For external use only. Do not use near eyes, inside of mouth, nose, on eyebrows or eye lashes. Consult a doctor if there are lice in these areas.

Stop use and ask doctor if eye, skin or scalp irritation occurs or continues.

Ask a doctor before use, if pregnant or nursing.

Keep out of reach of children. In case of ingestion, call Poison Control Center hotline immediently at 1-800-222-1222.

DOSAGE AND ADMINISTRATION

Directions: Read warnings and directions completely. For adults and children 12 months of age or older.

APPLY:

1. LIGHTLY dampen hair.

2. Liberally apply Lice Ladies EVICT to the hair, working down the entire scalp.

3. Wait 5 minutes. Do not dry hair.

4. Section the hair off into small sections.

5. Thoroughly comb through each section, with the Lice Ladies Evict Comb, ensuring each section is saturated with Lice Ladies EVICT, paying attention to the scalp area. Comb each section thoroughly, in four directions from scalp, all the way through to the hair ends.

6. As comb fills up with product, rinse with warm water or wipe onto paper towel.

7. Comb each section, re-applying Lice Ladies EVICT to saturate each new section and continue until each section combs clean.

8. Once treatment is complete, rinse hair thoroughly, protecting the eyes with a towel or wash cloth. Cleanse hair with your daily regiment shampoo to ensure hair is clean after treatment.

FOLLOW UP:

9. Repeat treatment in 7-10 days to ensure there has not been a reinfestation.

10. Use Lice Ladies PREVENT Natural Daily Lice Prevention Spray daily to aid in the prevention of new head lice infestations.

INACTIVE INGREDIENT

Inactive Ingredients: Benzyl alcohol, coco betaine (derived from coconuts), dimethicone peppermint oil (mentha piperita), purified water, protease enzyme.

PACKAGE LABEL

Lice Ladies

Evict

Natural Lice Treatment Mousse

Evict lice out of hair

safe and effectively!

Natural formula mousse aiding in treatment of symptoms and removal of head lice and nits.

Non-Toxic, Pesticide Free, Pleasant Frangrance.

FL OZ [GALLON] ML

Natural Lice Treament Mousse